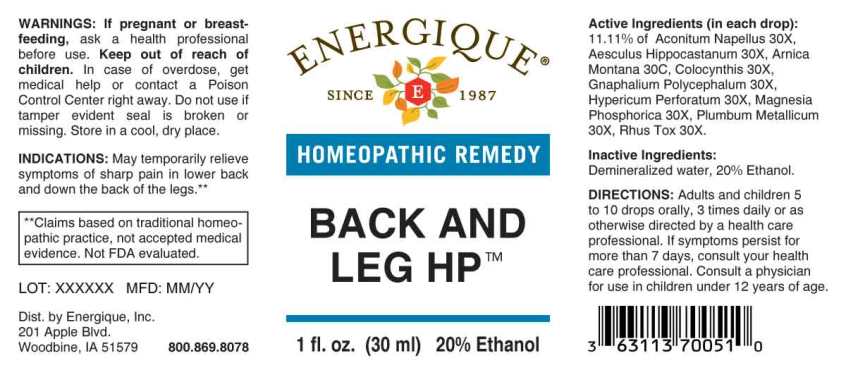 DRUG LABEL: Back and Leg HP
NDC: 44911-0624 | Form: LIQUID
Manufacturer: Energique, Inc.
Category: homeopathic | Type: HUMAN PRESCRIPTION DRUG LABEL
Date: 20231130

ACTIVE INGREDIENTS: ACONITUM NAPELLUS WHOLE 30 [hp_X]/1 mL; HORSE CHESTNUT 30 [hp_X]/1 mL; CITRULLUS COLOCYNTHIS FRUIT PULP 30 [hp_X]/1 mL; PSEUDOGNAPHALIUM OBTUSIFOLIUM WHOLE 30 [hp_X]/1 mL; HYPERICUM PERFORATUM WHOLE 30 [hp_X]/1 mL; MAGNESIUM PHOSPHATE, DIBASIC TRIHYDRATE 30 [hp_X]/1 mL; LEAD 30 [hp_X]/1 mL; TOXICODENDRON PUBESCENS LEAF 30 [hp_X]/1 mL; ARNICA MONTANA WHOLE 30 [hp_X]/1 mL
INACTIVE INGREDIENTS: WATER; ALCOHOL

DRUG FACTS:

ACTIVE INGREDIENTS:

(in each drop): 11.11% of Aconitum Napellus 30X, Aesculus Hippocastanum 30X, Arnica Montana 30C Colocynthis 30X, Gnaphalium Polycephalum 30X, Hypericum Perforatum 30X, Magnesia Phosphorica 30X, Plumbum Metallicum 30X, Rhus Tox 30X.

INDICATIONS:

May temporarily relieve symptoms of sharp pain in lower back and down the back of the legs and bursitis.**

**Claims based on traditional homeopathic practice, not accepted medical evidence. Not FDA evaluated.

WARNINGS:

If pregnant or breast-feeding, ask a health professional before use.

Keep out of reach of children. In case of overdose, get medical help or contact a Poison Control Center right away.

Do not use if tamper evident seal is broken or missing. Store in a cool, dry place.

KEEP OUT OF REACH OF CHILDREN:

In case of overdose, get medical help or contact a Poison Control Center right away.

DIRECTIONS:

Adults and children 5 to 10 drops orally, 3 times daily or as otherwise directed by a health care professional. If symptoms persist for more than 7 days, consult your health care professional.

Consult a physician for use in children under 12 years of age.

INDICATIONS:

May temporarily relieve symptoms of sharp pain in lower back and down the back of the legs and bursitis.**

**Claims based on traditional homeopathic practice, not accepted medical evidence. Not FDA evaluated.

INACTIVE INGREDIENTS:

Demineralized water, 20% Ethanol.

QUESTIONS:

Dist. by Energique, Inc.

201 Apple Blvd

Woodbine, IA 51579 800.869.8078

PACKAGE LABEL DISPLAY:

ENERGIQUE
SINCE 1987
HOMEOPATHIC REMEDY
BACK AND LEG HP
1 fl. oz. (30 ml)